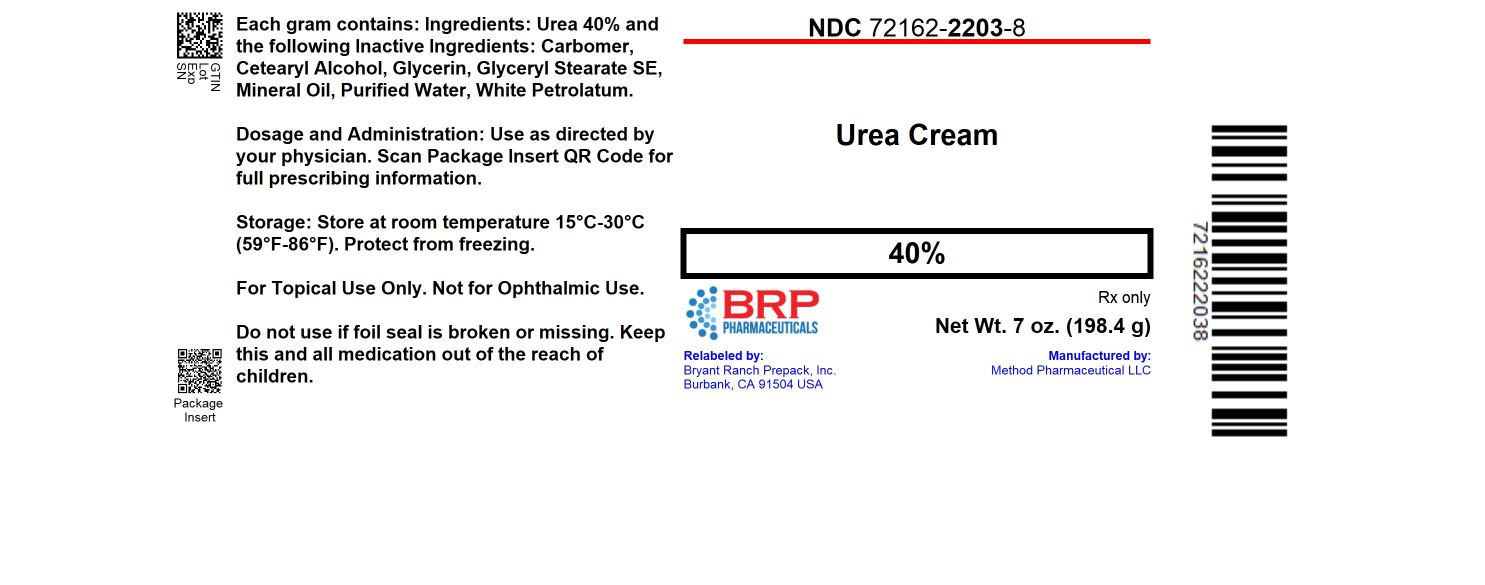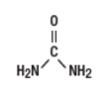 DRUG LABEL: Urea Cream 40 Percent
NDC: 72162-2203 | Form: CREAM
Manufacturer: Bryant Ranch Prepack
Category: prescription | Type: HUMAN PRESCRIPTION DRUG LABEL
Date: 20260213

ACTIVE INGREDIENTS: UREA 400 mg/1 g
INACTIVE INGREDIENTS: GLYCERIN; CARBOMER HOMOPOLYMER, UNSPECIFIED TYPE; CETYL ALCOHOL; WHITE PETROLATUM; MINERAL OIL; WATER; GLYCERYL STEARATE SE

Urea 40 Percent Cream

Description

Urea 40% is a keratolytic emollient which is a gentle, yet potent, tissue softener for nails and/or skin. Each gram of Urea 40% contains 40% urea as an active ingredient, and the following inactive ingredients:

Carbomer, Cetearyl Alcohol, Glycerin, Glyceryl Stearate SE, Mineral Oil, Purified Water, White Petrolatum.

Urea is a diamide of carbonic acid with the following chemical structure:

Clinical Pharmacology

Urea gently dissolves the intercellular matrix which results in loosening the horny layer of skin and shedding scaly skin at regular intervals, thereby softening hyperkeratotic areas of the skin.

Pharmacokinetics

The mechanism of action of topically applied urea is not yet known.

Indications and Usage

For debridement and promotion of normal healing of hyperkeratotic surface lesions, particularly where healing is retarded by local infection, necrotic tissue, fibrinous or purulent debris or eschar. Urea is useful for the treatment of hyperkeratotic conditions such as dry, rough skin, dermatitis, psoriasis, xerosis, ichthyosis, eczema, keratosis pilaris, keratosis palmaris, keratoderma, corns and calluses, as well as damaged, ingrown and devitalized nails.

Contraindications

Known hypersensitivity to any of the listed ingredients.

Warnings

For topical use only. Avoid contact with eyes, lips or mucous membranes.

Precautions

This medication is to be used as directed by a physician and should not be used to treat any condition other than that for which it was prescribed. If redness or irritation occurs, discontinue use and consult a physician.

PREGNANCY: Pregnancy Category B. Animal reproduction studies have revealed no evidence of harm to the fetus, however, there are no adequate and well-controlled studies in pregnant women. Because animal reproductive studies are not always predictive of human response, Urea 40% should be given to a pregnant woman only if clearly needed.

NURSING MOTHERS: It is not known whether or not this drug is excreted in human milk. Because many drugs are excreted in human milk, caution should be exercised when Urea 40% is administered to a nursing woman.

Adverse Reactions

Transient stinging, burning, itching or irritation may occur and normally disappear upon discontinuing the use of this product.

To report SUSPECTED ADVERSE REACTIONS, contact Method Pharmaceuticals, LLC at

1-877-250-3427; or FDA at 1-800-FDA-1088 or www.fda.gov/medwatch.

Dosage and Administration

Apply Urea 40% to affected skin twice per day, or as directed by your physician. Rub in until completely absorbed.

Apply to diseased or damaged nail(s) twice per day, or as directed by a physician.

How Supplied

Urea 40% Cream

3 oz. (85 g): NDC 72162-2203-4

1 oz. (28.35 g): NDC 72162-2203-7

7 oz. (198.4 g): NDC 72162-2203-8

Store at room temperature 15°C - 30°C (59°F-86°F). Protect from freezing. Keep bottle tightly closed.

KEEP THIS AND ALL MEDICATIONS OUT OF THE REACH OF CHILDREN.

Repackaged/Relabeled by:
Bryant Ranch Prepack, Inc.
Burbank, CA 91504

Manufactured for:

Method Pharmaceuticals, LLC

Southlake, Texas 76092

Rev. 09/23

PACKAGE LABEL

Urea Cream 40%